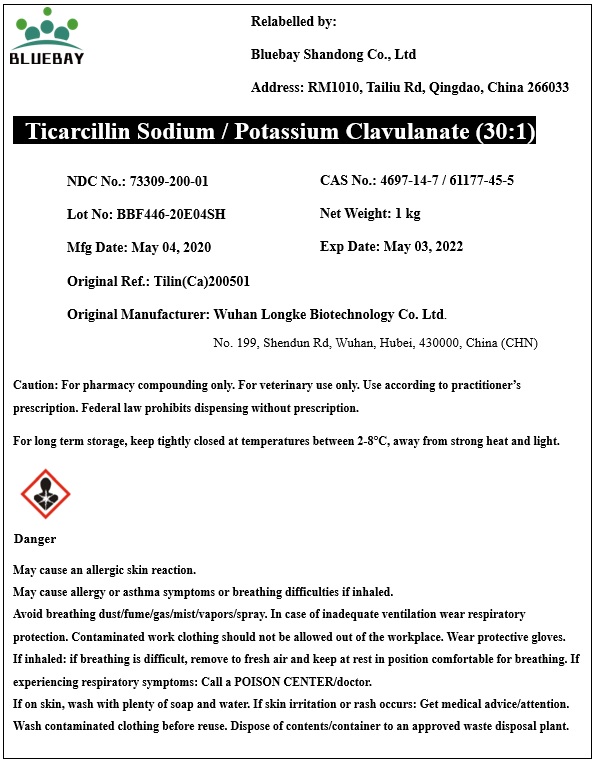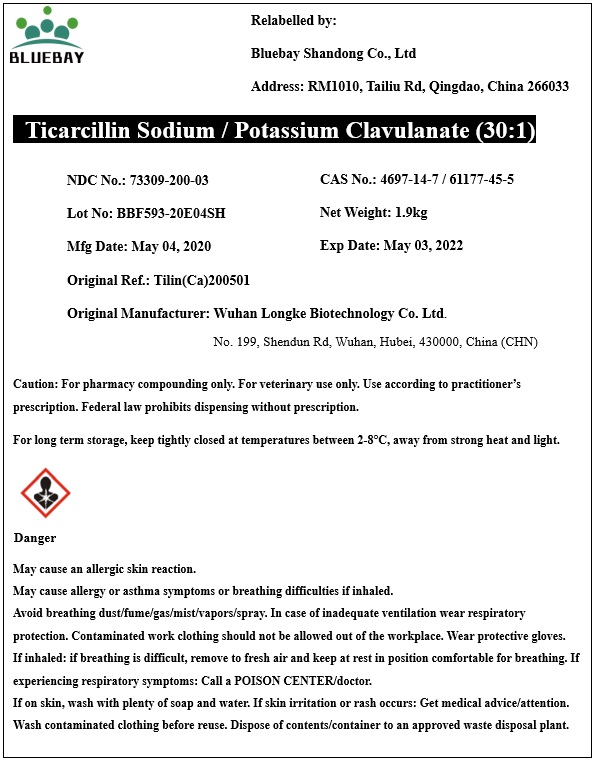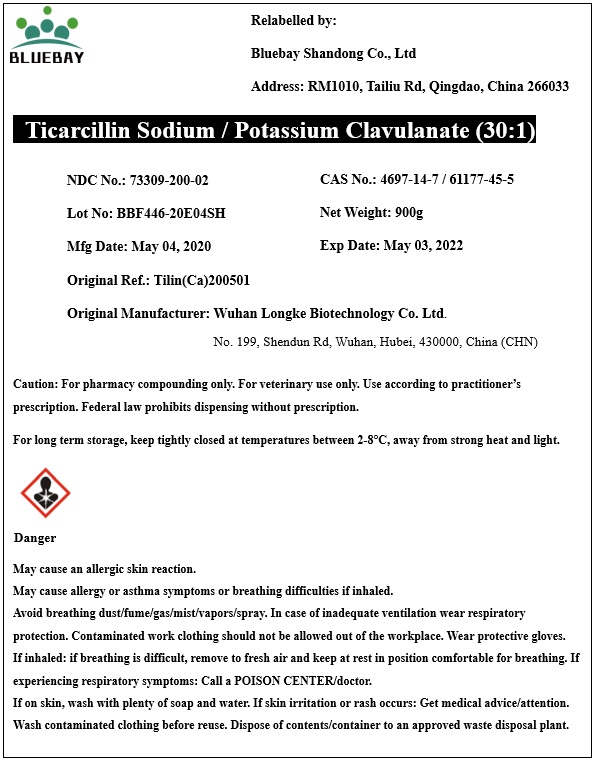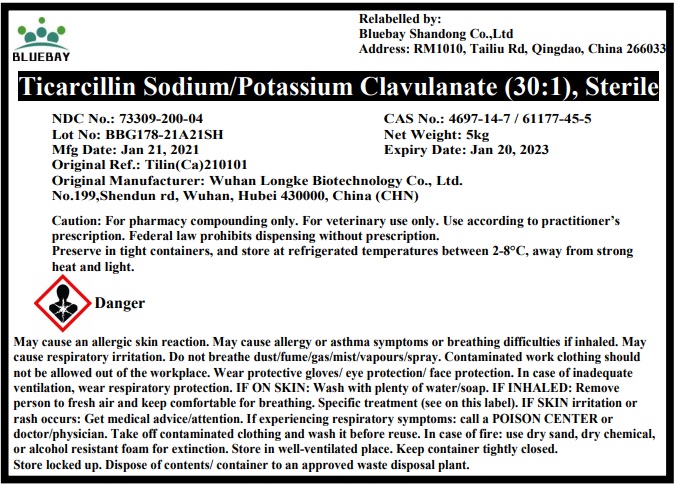 DRUG LABEL: Ticarcillin Sodium/Potassium Clavulanate
NDC: 73309-200 | Form: POWDER
Manufacturer: BLUEBAY SHANDONG CO.,LTD
Category: other | Type: BULK INGREDIENT
Date: 20210415

ACTIVE INGREDIENTS: TICARCILLIN DISODIUM 0.968 kg/1 kg; CLAVULANATE POTASSIUM 0.032 kg/1 kg

Ticarcillin Sodium / Potassium Clavulanate